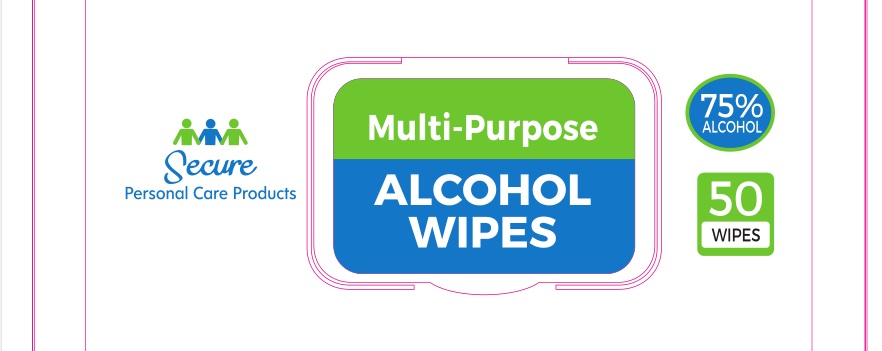 DRUG LABEL: secure personal care products alcohol wipes
NDC: 73703-127 | Form: CLOTH
Manufacturer: Secure Personal Care Products LLC
Category: otc | Type: HUMAN OTC DRUG LABEL
Date: 20231024

ACTIVE INGREDIENTS: ALCOHOL 75 g/100 g; BENZALKONIUM CHLORIDE 0.05 g/100 g
INACTIVE INGREDIENTS: WATER; GLYCERIN; ALOE VERA LEAF

73703-127 secure personal care products alcohol wipes

INGREDIENTS:

Alcohol, Aqua (Purified & De-Ionized Water), Glycerin, Benzalkonium Chloride, Aloe Barbadensis Leaf Extract

PURPOSE

THESE WIPES DO NOT REPLACE WIPES USED FOR MEDICAL PROCEDURES. THESE WIPES ARE MEANT FOR GENERAL CLEANSING.

INDICATIONS AND USAGE

THESE WIPES DO NOT REPLACE WIPES USED FOR MEDICAL PROCEDURES. THESE WIPES ARE MEANT FOR GENERAL CLEANSING.

Keep this out of reach of children.

DOSAGE AND ADMINISTRATION

˙ For external use only.

˙ THESE WIPES DO NOT REPLACE WIPES USED FOR MEDICAL PROCEDURES. THESE WIPES ARE MEANT FOR GENERAL CLEANSING.

WARNINGS

˙ For external use only.

˙ THESE WIPES DO NOT REPLACE WIPES USED FOR MEDICAL PROCEDURES. THESE WIPES ARE MEANT FOR GENERAL CLEANSING.

˙ Keep in a dry place away from fire.

˙ Keep this out of reach of children.

˙ If swallowed, get medical help or contact a Poision Control Center immediately.

˙ Do not use in or contact the eyes.

˙ Discontinue use if irritation and redness develop. If the condition persists for more than 72 hours, consult a physician.

˙ Please close the lid after dispensing to maintain purity. Alcohol by nature evaporates quickly.

˙ Store below 95℉ (35 ℃)

INGREDIENTS:

Alcohol, Aqua (Purified & De-Ionized Water), Glycerin, Benzalkonium Chloride, Aloe Barbadensis Leaf Extract

PDP

50 wipes, NDC: 73703-127-01